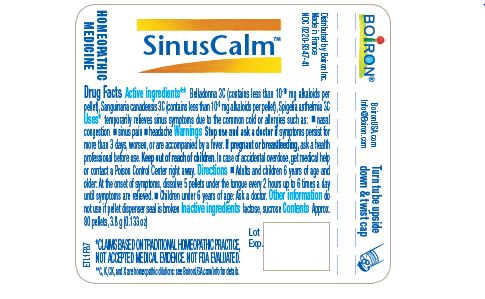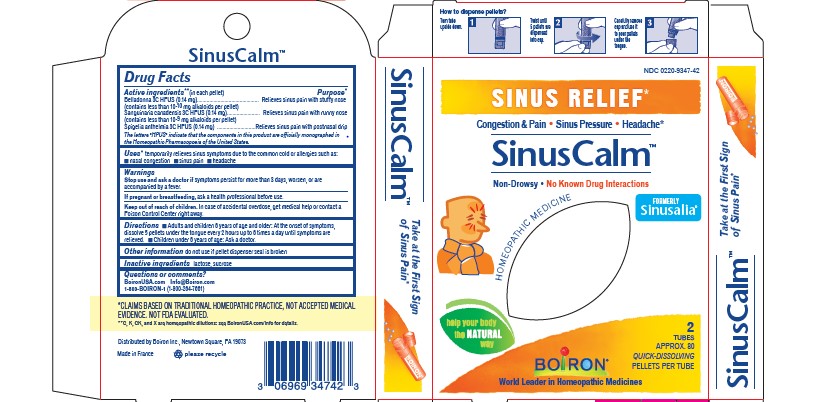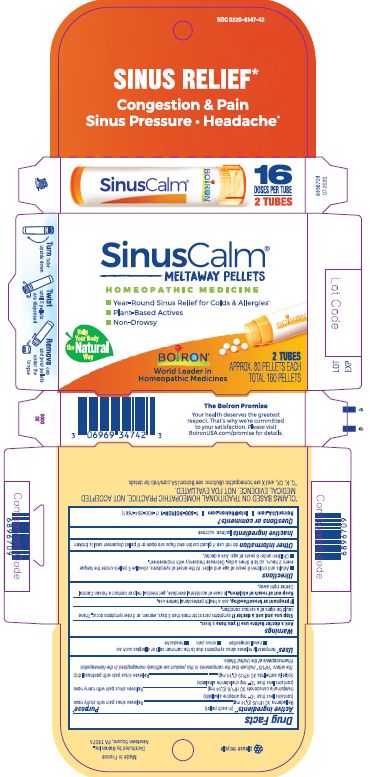 DRUG LABEL: SinusCalm
NDC: 0220-9347 | Form: PELLET
Manufacturer: Boiron
Category: homeopathic | Type: HUMAN OTC DRUG LABEL
Date: 20231030

ACTIVE INGREDIENTS: SANGUINARIA CANADENSIS ROOT 3 [hp_C]/1 1; ATROPA BELLADONNA 3 [hp_C]/1 1; SPIGELIA ANTHELMIA 3 [hp_C]/1 1
INACTIVE INGREDIENTS: LACTOSE, UNSPECIFIED FORM; SUCROSE

SinusCalm

ACTIVE INGREDIENT

Belladonna 3C HPUS (0.14 mg), Sanguinaria canadensis 3C HPUS (0.14 mg), Spigelia anthelmia 3C HPUS(0.14 mg) **
(in each pellet)

PURPOSE

Belladonna 3C HPUS Relieves sinus pain and stuffy nose*

(contains less than 10^-9 mg atropine alkaloids per pellet)

Sanguinaria canadensis 3C HPUS Relieves sinus pain with runny hose*

(contains less than 10-^8 mg chelidonine alkaloids per pellet)

Spigelia anthelmia 3C HPUS Relieves sinus pain with postnasal drip*

The letters "HPUS" indicate that the components in this product are officially monographed in the Homeopathic Pharmacopoeia of the United States.

INDICATIONS AND USAGE

Temporarily relieves sinus symptoms due to the common cold or allergies such as: nasal congestion, sinus pain, headache

Ask a doctor before use if you have a fever

Stop use and ask a doctor if symptoms persist for more than 3 days, worsen, or if new symptoms occur. These could be signs of a serious condition.

PREGNANCY OR BREAST FEEDING

If pregnant or breastfeeding, ask a health professional before use.

Keep out of reach of children. In case of accidental overdose, get medical help or contact a Poison Control Center right away.

DOSAGE AND ADMINISTRATION

Adults and children 6 years of age and older: At the onset of symptoms, dissolve 5 pellets under the tongue every 2 hours up to 6 times a day until symptoms are relieved. Decrease frequency with improvement. Children under 6 years of age: Ask a doctor.

do not use if glued carton end flaps are open or if pellet dispenser seal is broken.

Contains approx 80 quick dissolving pellets per tube.
How to dispense pellets? Turn tube upside down. Twist until 5 pellets are dispensed into cap. Carefully remove the cap and use it to pour pellets under the tongue.

Tubes contains approx. 80 pellets, 3.8 g (0.13 oz)

2 Tubes

16 Doses per tube

Year-round sinus relief for colds & allergies

Plant-based actives

Non-drowsy

Formally Sinusalia

Do not use if glued carton and flaps are open or if pellet dispenser seal is broken.
*CLAIMS BASED ON TRADITIONAL HOMEOPATHIC PRACTICE NOT ACCEPTED MEDICAL EVIDENCE. NOT FDA EVALUATED.
*C,K,CK, and X are homeopathic dilutions: see BoironUSA.com/info for details.

INACTIVE INGREDIENT

lactose, sucrose

QUESTIONS

1-800-BOIRON-1 (1-800-264-7661),
BoironUSA.com Info@boiron.com
Distributed by Boiron, Inc. Newtown Square, PA 19073

Made in France